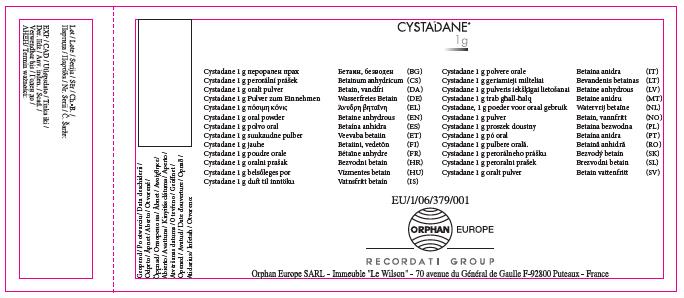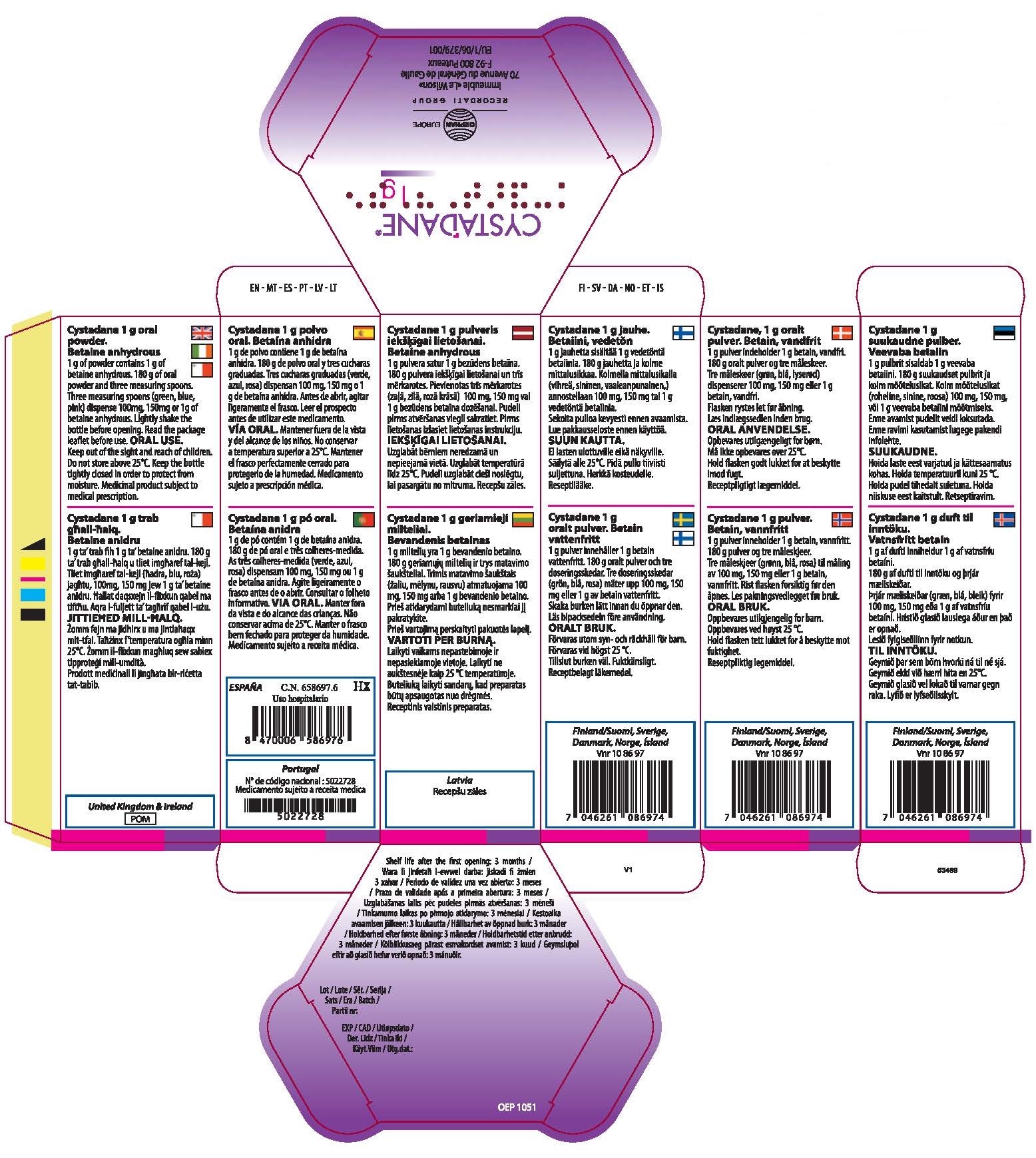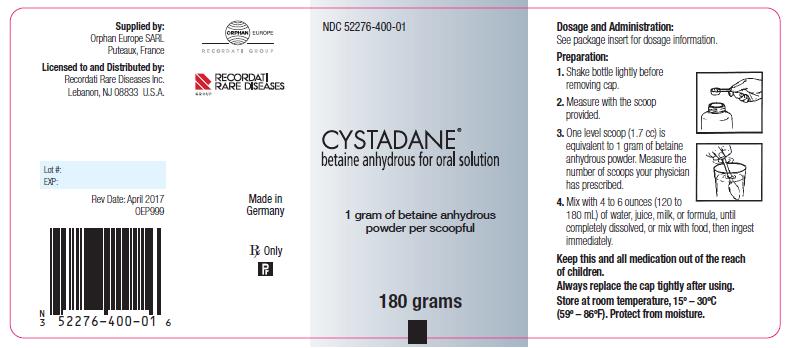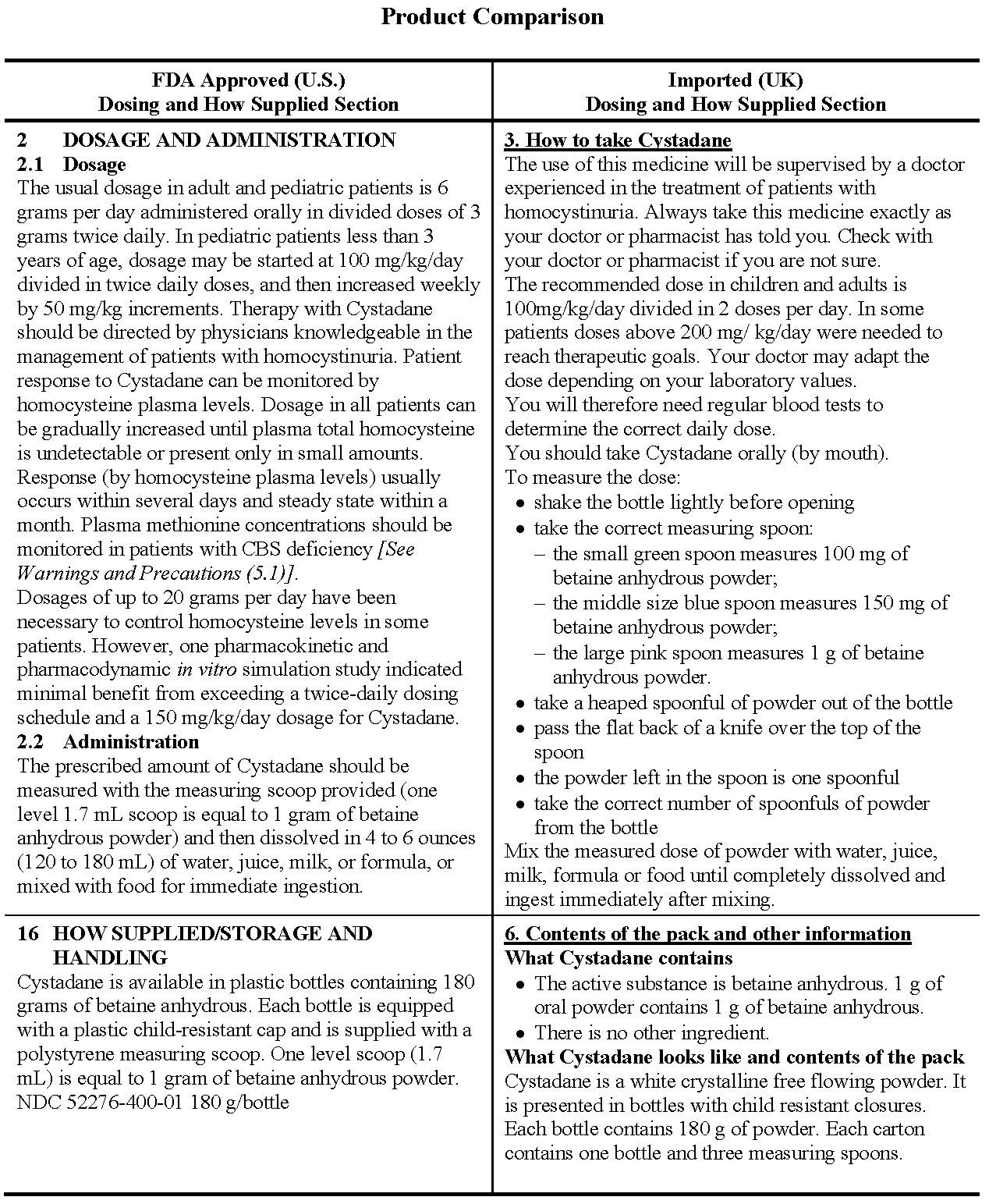 DRUG LABEL: Cystadane
NDC: 52276-401 | Form: POWDER, FOR SOLUTION
Manufacturer: Orphan Europe SARL
Category: prescription | Type: HUMAN PRESCRIPTION DRUG LABEL
Date: 20180305

ACTIVE INGREDIENTS: BETAINE 1 g/1 g

Package leaflet: Information for the patient

Read all of this leaflet carefully before you start taking this medicine because it contains important information for you.

- Keep this leaflet. You may need to read it again.
- If you have any further questions, ask your doctor or your pharmacist.
- This medicine has been prescribed for you only. Do not pass it on to others. It may harm them, even if their signs of illness are the same as yours.
- If you get any side effects, talk to your doctor or pharmacist. This includes any possible side effects not listed in this leaflet. See section 4.

What is in this leaflet

1. What Cystadane is and what it is used for
2. What do you need to know before you take Cystadane
3. How to take Cystadane
4. Possible side effects
5. How to store Cystadane
6. Contents of the pack and other information

1. What Cystadane is and what it is used for

Cystadane contains betaine anhydrous which is intended to be an adjunctive treatment of homocystinuria, an inherited (genetic) disease where the amino acid methionine cannot be broken down completely by the body.
Methionine is present in regular food protein (e.g. meat, fish, milk, cheese, eggs). It is converted into homocysteine which is then normally converted into cysteine during digestion. Homocystinuria is a disease caused by the accumulation of homocysteine which is not converted to cysteine and is characterised by formation of clots in the veins, bone weakness, and skeletal and crystalline lens abnormalities. The use of Cystadane together with other treatments such as vitamin B6, vitamin B12, folate and a specific diet aims to reduce the elevated homocysteine levels in your body.
2. What you need to know before you take Cystadane
Do not take Cystadane
If you are allergic to betaine anhydrous.
Warnings and precautions
Talk to your doctor or pharmacist before taking Cystadane.
If you notice side effects like headaches, vomiting or a change in your vision and you are of the homocystinuria subtype called CBS (cystathionine beta-synthase deficiency), please contact your doctor immediately, they could be signs of a swelling in the brain (cerebral oedema). In that case your doctor will monitor your methionine level in your body and may review your diet. Your treatment with Cystadane may need to be interrupted.
If you are treated with Cystadane and with an amino-acid mixture and if you need to take other medicines at the same time, leave 30 minutes between the intake (see “section “Other medicines and Cystadane”).
Other medicines and Cystadane
Tell your doctor if you are taking, have recently taken or might take any other medicines.
If you are taking amino-acid mixture or medicines such as vigabatrin or Gaba analogues (medicine used to treat epilepsy), please tell your doctor as they might interact with your treatment with Cystadane.
Pregnancy and breast-feeding
If you are pregnant or breast-feeding, think you may be pregnant or are planning to have a baby, ask your doctor for advice before taking this medicine. Your doctor will decide if you can use this medicine during pregnancy and breast-feeding.
Driving and using machines
Cystadane has no or negligible influence on the ability to drive and use machines.

3. How to take Cystadane
The use of this medicine will be supervised by a doctor experienced in the treatment of patients with homocystinuria.
Always take this medicine exactly as your doctor or pharmacist has told you. Check with your doctor or pharmacist if you are not sure.
The recommended dose in children and adults is 100mg/kg/day divided in 2 dosesper day. In some patients doses above 200 mg/kg/day were needed to reach therapeutic goals. Your doctor may adapt the dose depending on your laboratory values.
You will therefore need regular blood tests to determine the correct daily dose.
You should take Cystadane orally (by mouth).
To measure the dose:

- shake the bottle lightly before opening
- take the correct measuring spoon:
  - the small green spoon measures 100 mg of betaine anhydrous powder;
  - the middle size blue spoon measures 150 mg of betaine anhydrous powder;
  - the large pink spoon measures 1 g of betaine anhydrous powder.
  - take a heaped spoonful of powder out of the bottle
  - pass the flat back of a knife over the top of the spoon
  - the powder left in the spoon is one spoonful
  - take the correct number of spoonfuls of powder from the bottle

Mix the measured dose of powder with water, juice, milk, formula or food until completely dissolved and ingest immediately after mixing.
If you take more Cystadane than you should
If you accidentally take too much Cystadane, talk to a doctor or pharmacist immediately.
If you forget to take Cystadane
Do not take a double dose to make up for forgotten doses. If you forget to take a dose take it as soon as you remember it and continue the next dose as planned.

If you stop taking Cystadane
Do not stop the treatment without consulting your doctor. Contact your doctor or pharmacist before stopping.
If you have any further questions on the use of this medicine, ask your doctor or pharmacist.
4. Possible side effects
Like all medicines, this medicine can cause side effects, although not everybody gets them.
The most commonly side effect when taking Cystadane which may affect more than 1 in 10 people (frequency very common) is elevated levels of methionine in the blood.
Methionine level can be related to swelling in the brain (cerebral swelling), which may affect up to 1 in 100 people (frequency uncommon). If you experience morning headaches with vomiting and/or visual changes, contact immediately your doctor (they could be signs of a swelling in the brain).

Gastrointestinal disorders like diarrhoea, nausea, vomiting, stomach discomfort and inflammation of the tongue may occur uncommonly (may affect up to 1 in 100 people).
Other uncommon side effects (may affect up to 1 in 100 people) may include decreased appetite (anorexia), agitation, irritability, hair loss, hives, skin odour abnormal, lack of control over passing urine (urinary incontinence).
Reporting of side effects
If you get any side effects, talk to your doctor or pharmacist. This includes any possible side effects not listed in this leaflet. You can also report side effects directly via the national reporting system listed in Appendix. By reporting side effects you can help provide more information on the safety of this medicine.
5. How to store Cystadane
Keep this medicine out of the sight and reach of children.
Do not use this medicine after the expiry date which is stated on the bottle label and the carton after EXP. The expiry date refers to the last day of that month.

Do not store above 25°C.
Keep the bottle tightly closed in order to protect from moisture. After the first opening of the bottle, the medicine should be used within 3 months.
Do not throw away any medicines via wastewater or household waste. Ask your pharmacist how to throw away medicines you no longer use. These measures will help protect the environment.
6. Contents of the pack and other information
What Cystadane contains

- The active substance is betaine anhydrous. 1 g of oral powder contains 1 g of betaine anhydrous.
- There is no other ingredient.

What Cystadane looks like and contents of the pack
Cystadane is a white crystalline free flowing powder. It is presented in bottles with child resistant closures. Each bottle contains 180 g of powder. Each carton contains one bottle and three measuring spoons.

Marketing Authorisation Holder
Orphan Europe SARL
Immeuble “Le Wilson”
70, avenue du General de Gaulle
F-92 800 Puteaux
France
Manufacturer
Orphan Europe SARL
Immeuble “Le Wilson”
70, avenue du Général de Gaulle
F-92800 Puteaux
France
For any information about this medicine, please contact the local representative of the Marketing Authorisation Holder.
This leaflet was last revised in 8/12/2016
Detailed information on this medicine is available on the European Medicines Agency web site: http://www.ema.europa.eu/. There are also links to other websites about rare diseases and treatments.

Orphan Europe Ltd. Tel : + 44 (0)14 9141 4333
United Kingdom - Ireland

APPENDIX

UNITED KINGDOM

Reporting of side effects
Yellow Card Scheme Website: www.mhra.gov.uk/yellowcard or search for MHRA Yellow Card in the Google Play or Apple App Store

Health Care Provider Letter

IMPORTANT PRESCRIBING INFORMATION

22 December 2017

Subject: Temporary importation of CYSTADANE® (betaine anhydrous for oral solution) to address impending shortage

Dear Health Care Provider,

There has been a manufacturing issue with the CYSTADANE® (betaine anhydrous for oral solution) approved for use and distribution in the United States (“U.S.-labeled CYSTADANE”), which has resulted in an interim shortage of this product in the U.S. market.

In order to alleviate the shortage of CYSTADANE in the U.S., Recordati Rare Diseases Inc. (Recordati) is coordinating with the U.S. Food and Drug Administration (FDA) to increase the availability of CYSTADANE. Recordati has initiated temporary importation of its CYSTADANE product approved for use in the United Kingdom into the U.S. market. This product is manufactured by Orphan Europe SARL in France. At this time, no other entity except Recordati, as the U.S. agent of Orphan Europe SARL, is authorized to import or distribute these products in the United States. FDA has not approved the product manufactured by Orphan Europe SARL’s manufacturing facility in France. The imported CYSTADANE is lot CYP1705. It will be dispensed by the U.S. specialty pharmacy, AnovoRx Group LLC.

There are some key differences between the FDA-approved CYSTADANE and the imported CYSTADANE.

- Measuring scoops: FDA-approved CYSTADANE is packaged with one scoop (white) that dispenses 1g of betaine anhydrous. Imported CYSTADANE is packaged with 3 measuring scoops (green, blue, and pink) that dispense 100mg, 150mg, or 1g of betaine anhydrous. The large 1g pink scoop in the imported CYSTADANE is equivalent to the white 1g scoop in the FDA-approved CYSTADANE. Patients should pay careful attention to use the appropriate scoop to take their prescribed dose. Please pass this information along to the patients. If the incorrect scoop is utilized, improper dosing may result, and the CYSTADANE treatment can be ineffective. This may result in an increased risk for cognitive disability and/or stroke due to the progression of the underlying disease.

- Dosing: The labeled dosing in the FDA-approved CYSTADANE is 6 grams/day in divided doses of 3 grams twice daily, and, for pediatric patients less than 3 years of age, dosage may be started at 100 mg/kg/day divided in twice daily doses and increased weekly by 50 mg/kg increments. The labeled dosing in the imported CYSTADANE is 100 mg/kg/day divided into 2 doses per day. Practitioners should be aware of these differences when prescribing and monitoring CYSTADANE.

A copy of the FDA-approved full prescribing information is being distributed with the imported CYSTADANE. Please refer to the FDA-approved package insert for full prescribing information. Storage conditions are the same as that of the FDA-approved product. Store at room temperature, 15º – 30ºC (59º – 86ºF). CYSTADANE is for oral use only. Protect from moisture. Keep this and all medications out of the reach of children.

U.S. FDA-approved Indication

CYSTADANE (betaine anhydrous for oral solution) is a methylating agent indicated for the treatment of homocystinuria to decrease elevated homocysteine blood levels. Included within the category of homocystinuria are:

- Cystathionine beta-synthase (CBS) deficiency
- 5,10-methylenetetrahydrofolate reductase (MTHFR) deficiency
- Cobalamin cofactor metabolism (cbl) defect

For reporting of adverse events and more information

Any adverse effects or medication issues resulting from the use of this drug or quality issues should be reported to Recordati Rare Diseases Inc. at 1-888-575-8344.

Adverse events or quality problems experienced with the use of this product may also be reported to the FDA's MedWatch Adverse Event Reporting program either online, by regular mail or by fax:

- Complete and submit the report Online: www.fda.gov/medwatch/report.htm
- Regular mail or Fax: Download form www.fda.gov/MedWatch/getforms.htm or call 1-800-332-1088 to request a reporting form, then complete and return to the address on the pre-addressed form, or submit by fax to 1-800-FDA-0178.

Important Safety Information

- Hypermethioninemia: CYSTADANE may worsen elevated plasma methionine concentrations in patients with CBS deficiency. Cerebral edema has been reported in patients receiving CYSTADANE.
- Monitoring: Monitor plasma methionine concentrations in patients with CBS deficiency. Keep plasma methionine concentrations below 1,000 μmol/L through dietary modification and, if necessary, a reduction of CYSTADANE dose.
- Most common adverse reactions (incidence > 2%) were nausea and gastrointestinal distress, based on physician survey.
- Pregnancy: Animal reproduction studies have not been conducted with CYSTADANE. Use only if clearly needed.
- Nursing women: It is not known whether CYSTADANE is excreted in human milk. Use only if clearly needed.
- Pediatrics: Pediatric patients ranging in age from 24 days to 17 years have been treated with CYSTADANE. Children younger than 3 years of age may benefit from dose titration.

We are committed to helping address patients’ unmet needs through our corporate mission. If you have questions or concerns regarding this product, please call AnovoRx Group, the specialty pharmacy that dispenses CYSTADANE, at 1‑888-487-4703 or Recordati Rare Diseases Medical Information at 1‑888-575-8344.

Steven R. Peltier

Vice President, Regulatory & Quality Compliance

Chief Compliance Officer

Recordati Rare Diseases Inc.

FDA-approved (U.S.) Bottle Label:

Imported (U.K.) Bottle Label:

Imported (U.K.) Carton:

Package/Label Display Panel

CYSTADANE®

1 g

Orphan Europe SARL

Immeuble “Le Wilson”

70 avenue du Général de Gaulle

F-92800 Puteaux

Cystadane 1 g oral powder.

Betaine anhydrous

1 g of powder contains 1 g of betaine anhydrous. 180 g of oral powder and three measuring spoons. Three measuring spoons (green, blue, pink) dispense 100mg, 150mg or 1g of betaine anhydrous. Lightly shake the bottle before opening. Read the package leaflet before use. ORAL USE. Keep out of the sight and reach of children. Do not store above 25°C. Keep the bottle tightly closed in order to protect from moisture. Medicinal product subject to medical prescription.

Shelf life after the first opening: 3 months

Lot:

EXP: